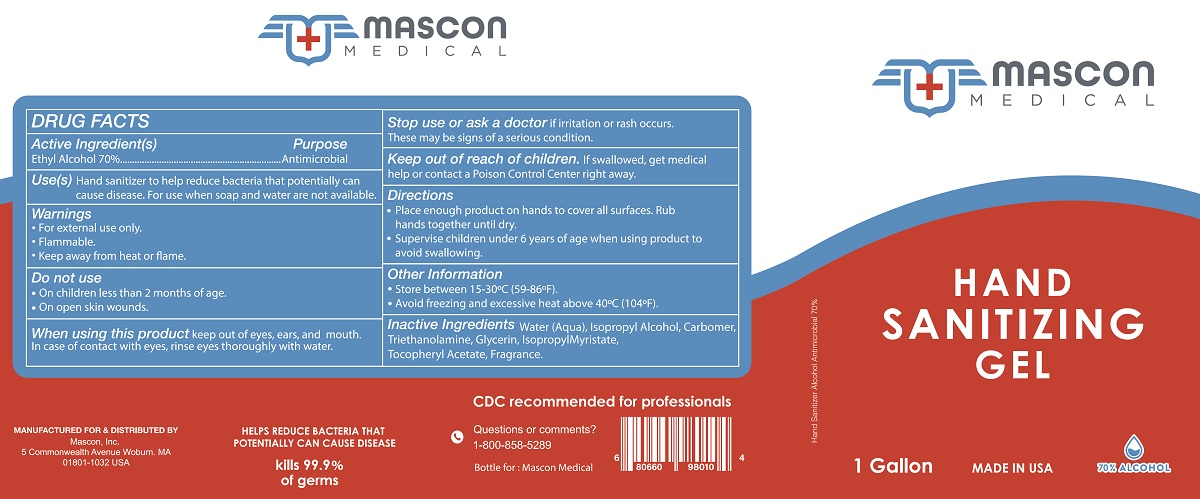 DRUG LABEL: Mascon Medical
NDC: 78593-200 | Form: GEL
Manufacturer: Mascon, Inc.
Category: otc | Type: HUMAN OTC DRUG LABEL
Date: 20200810

ACTIVE INGREDIENTS: ALCOHOL 0.7 mL/1 mL
INACTIVE INGREDIENTS: ISOPROPYL MYRISTATE; CARBOMER HOMOPOLYMER, UNSPECIFIED TYPE; WATER; TROLAMINE; GLYCERIN; ISOPROPYL ALCOHOL; .ALPHA.-TOCOPHEROL

Mascon Medical Hand Sanitizing Gel

Active Ingredient(s)

Ethyl Alcohol 70%

Purpose

Antimicrobial

Use(s)

Hand sanitizer to help reduce bacteria that potentially can cause disease. For use when soap and water are not available.

Warnings

- For external use only.
- Flammable.
- Keep away from heat or flame.

Do not use

- On children less than 2 months of age.
- On open skin wounds.

WHEN USING

When using this productkeep out of eyes, ears, and mouth. In case of contact with eyes, rinse eyes thoroughly with water.

Stop use or ask a doctor if irritation or rash occurs. These may be signs of a serious condition.

Keep out of reach of children. If swallowed, get medical help or contact a Poison Control Center right away.

Directions

- Place enough product on hands to cover all surfaces. Rub hands together until dry.
- Supervise children under 6 years of age when using product to avoid swallowing.

Other Information

- Store between 15-30°C (59-86°F).
- Avoid freezing and excessive heat above 40°C (104°F).

INACTIVE INGREDIENT

Inactive Ingredients Water (Aqua), Isopropyl Alcohol, Carbomer, Triethanolamine, Glycerin, Isopropyl Myristate, Tocopheryl Acetate, Fragrance.

PACKAGE LABEL

Mascon Medical

Hand Sanitizing Gel

1 Gallon

NDC 78593-200-00